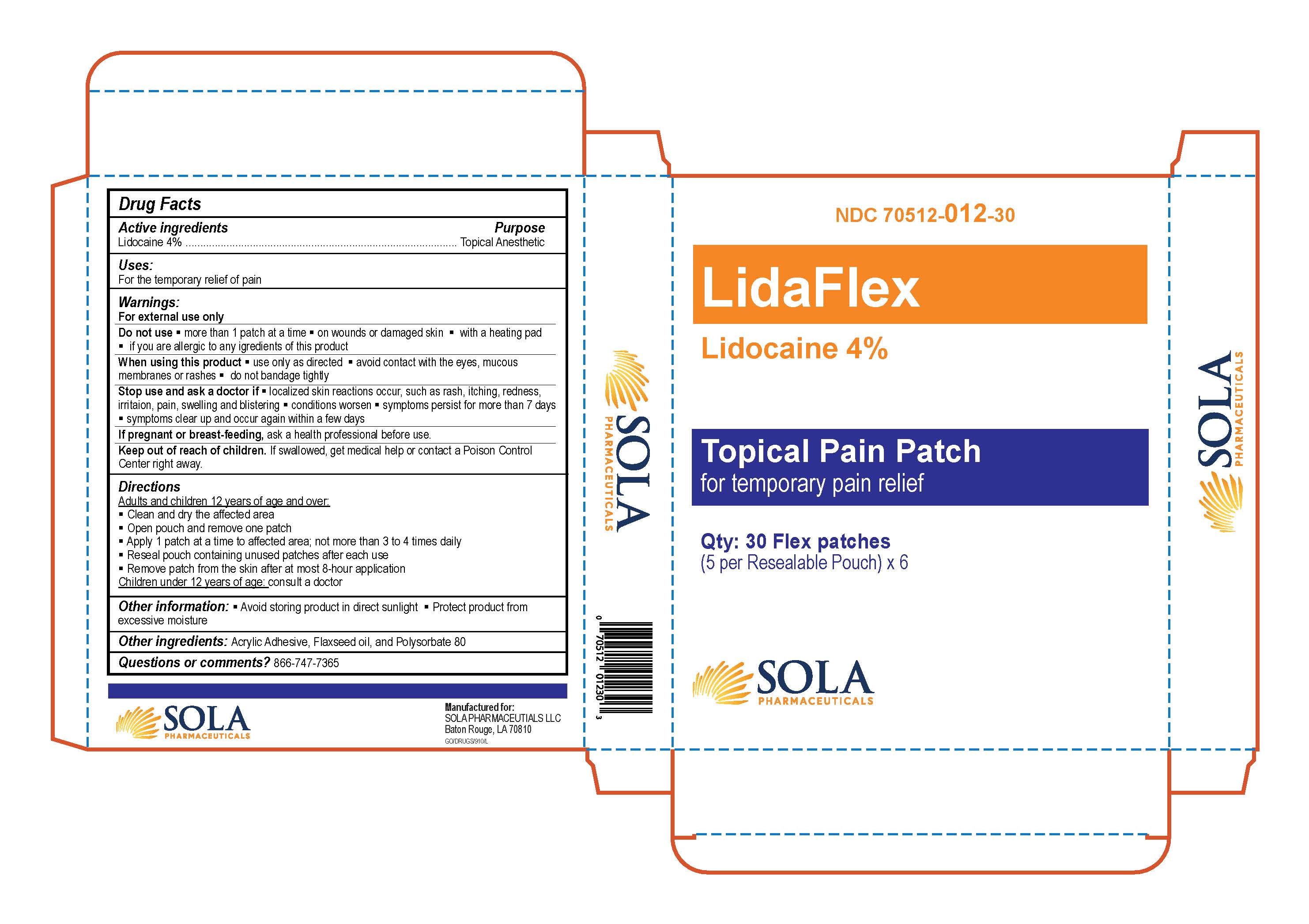 DRUG LABEL: LidaFlex
NDC: 70512-012 | Form: PATCH
Manufacturer: SOLA Pharmaceuticals
Category: otc | Type: HUMAN OTC DRUG LABEL
Date: 20251208

ACTIVE INGREDIENTS: LIDOCAINE 40 mg/1 g
INACTIVE INGREDIENTS: POLYSORBATE 80; FLAX SEED; ACRYLIC ACID

LidaFlex

Active ingredients:

Lidocaine 4%

Purpose:

Topical Anesthetic

Uses:

For temporary relief of pain

Warnings:

For external use only

Do not use

- More than 1 pathch at a time
- On wounds or damaged skin
- With a heating pad
- If you are allergic to any ingredients of this product

When using this product

- Use only as directed
- Avoid contact with the eyes, mucous membranes or rashes
- Do not bandage tightly

Stop use and ask a doctor if

- localized skin reactions occur, such as rash, itching, redness, irritation, pain, swelling and blistering
- Conditions worsen
- Symptoms persist for more than 7 days
- Symptoms clear up and occur again within a few days

If Pregnant or breast-feeding

Ask a health professional before use.

Keep out of reach of children

If swallowed, get medical help or contact a Poison Control Center right away.

Directions

Adults and Children 12 years of age and over:

- Clean and dry the affected area
- Open pouch and remove one patch
- Apply 1 patch at a time to affected area; not more than 3 to 4 times daily
- Reseal pouch containing unused patches after each use
- Remove patch from the skin after at most 8-hour application

Children under 12 years of age: Consult a doctor

Other information:

- Avoid storing product in direct sunlight
- Protect product from exceessive moisture

INACTIVE INGREDIENT

Acrylic Adhesive, Flaxseed oil, and Polysorbate 80

PACKAGE LABEL

Manufactured for:

SOLA Pharmaceuticals

655 Highlandia Dr. Ste B

Baton Rouge, LA 70810

For questions for comments call 866-747-7365

LidaFlex Patch

Topical Pain Patch

For temporay pain relief

NDC 70512-012-30

Qty: 30 Flex Patches

(5 per Resealable Pouch) x 6